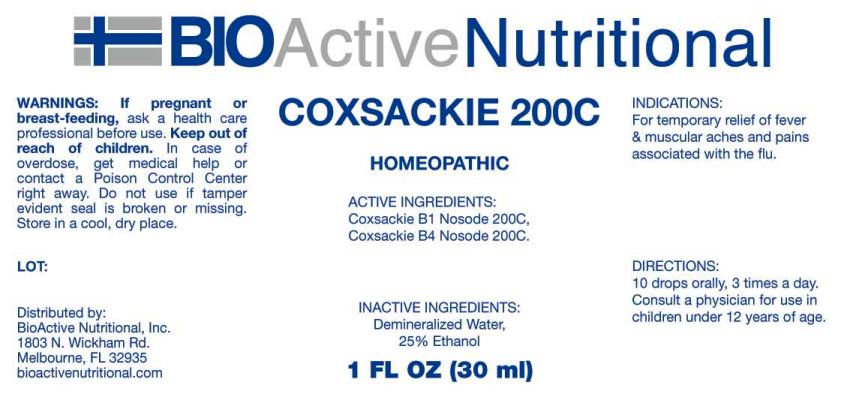 DRUG LABEL: Coxsackie
NDC: 43857-0111 | Form: LIQUID
Manufacturer: BioActive Nutritional, Inc.
Category: homeopathic | Type: HUMAN OTC DRUG LABEL
Date: 20160414

ACTIVE INGREDIENTS: HUMAN COXSACKIEVIRUS B1 200 [hp_C]/1 mL; HUMAN COXSACKIEVIRUS B4 200 [hp_C]/1 mL
INACTIVE INGREDIENTS: WATER; ALCOHOL

Drug Facts:

ACTIVE INGREDIENTS:

Coxsackie B1 Nosode 200C, Coxsackie B4 Nosode 200C.

INDICATIONS:

For temporary relief of fever and muscular aches and pains associated with the flu.

WARNINGS:

If pregnant or breast-feeding, ask a health care professional before use.

Keep out of reach of children. In case of overdose, get medical help or contact a Poison Control Center right away.

Do not use if tamper evident seal is broken or missing. Store in cool, dry place.

DIRECTIONS:

10 drops orally, 3 times a day. Consult a physician for use in children under 12 years of age.

INACTIVE INGREDIENTS:

Demineralized water, 25% Ethanol.

Keep out of reach of children. In case of overdose, get medical help or contact a Poison Control Center right away.

INDICATIONS:

For temporary relief of fever and muscular aches and pains associated with the flu.

QUESTIONS:

Distributed by:

BioActive Nutritional, Inc.

1803 N. Wickham Rd.

Melbourne, FL 32935

bioactivenutritional.com

PACKAGE LABEL DISPLAY:

BIOActive Nutritional

COXSACKIE 200C

HOMEOPATHIC

1 FL OZ (30 ml)